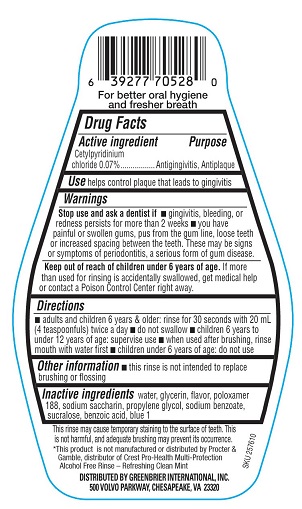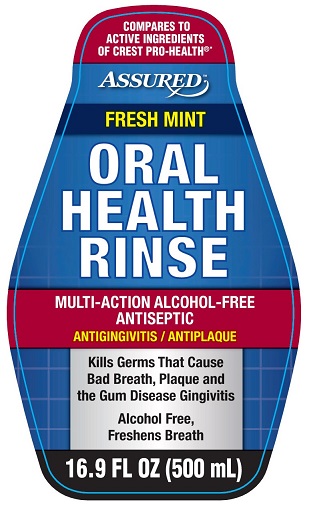 DRUG LABEL: Assured
NDC: 33992-0320 | Form: RINSE
Manufacturer: Greenbrier International, Inc.
Category: otc | Type: HUMAN OTC DRUG LABEL
Date: 20210823

ACTIVE INGREDIENTS: CETYLPYRIDINIUM CHLORIDE 0.07 g/100 mL
INACTIVE INGREDIENTS: SODIUM BENZOATE; SUCRALOSE; WATER; BENZOIC ACID; POLOXAMER 188; GLYCERIN; SACCHARIN SODIUM; FD&C BLUE NO. 1; PROPYLENE GLYCOL

Assured Fresh Mint Oral Health Rinse

For better oral hygiene and fresher breath

Drug Facts

Active ingredient
Cetylpyridinium chloride 0.07%

Purpose

Antigingivitis, Antiplaque

INDICATIONS AND USAGE

Usehelps control plaque that leads to gingivitis

Warnings

Stop use and ask a dentist if

- gingivitis, bleeding, or redness persists for more than 2 weeks
- you have painful or swollen gums, pus from the gum line, loose teeth or increased spacing between the teeth. These may be symptoms of periodontitis, a serious form of gum disease.

Keep out of reach of children under 6 years of age. If more than used for rinsing is accidentally swallowed, get medical help or contact a Poison Control Center right away.

Directions

- adults and children 6 years & older: rinse for 30 seconds with 20 mL (4 teaspoonfuls) twice a day
- do not swallow
- children 6 to under 12 years of age: supervise use
- when used after brushing. rinse mouth with water first
- children under 6 years of age: do not use

Other information

- this rinse is not intended to replace brushing or flossing

INACTIVE INGREDIENT

Inactive ingredients water, glycerin, flavor, poloxamer 188, sodium saccharin, propylene glycol, sodium benzoate, sucralose, benzoic acid, blue 1

This rinse may cause temporary staining to the surface of the teeth. This is not harmful, and adequate brushing may prevent its occurrence.

*This product is not manufactured or distributed by Proctor & Gamble, distributor of Crest Pro-Health Multi-Protection Alcohol Free Rinse - Refreshing Clean Mint.

DISTRIBUTED BY: GREENBRIER INTERNATIONAL INC.

500 VOLVO PARKWAY, CHESAPEAKE, VA 23320

PACKAGE LABEL

COMPARES TO ACTIVE INGREDIENTS OF CREST PRO-HEALTH®*

Assured™

FRESH MINT

ORAL HEALTH RINSE

MULTI-ACTION ALCOHOL-FREE ANTISEPTIC

ANTIGINGIVITIS / ANTIPLAQUE

Kills Germs that Cause Bad Breath, Plaque and the Gum Disease Gingivitis

Alcohol Free, Freshens Breath

16.9 FL OZ (500 mL)